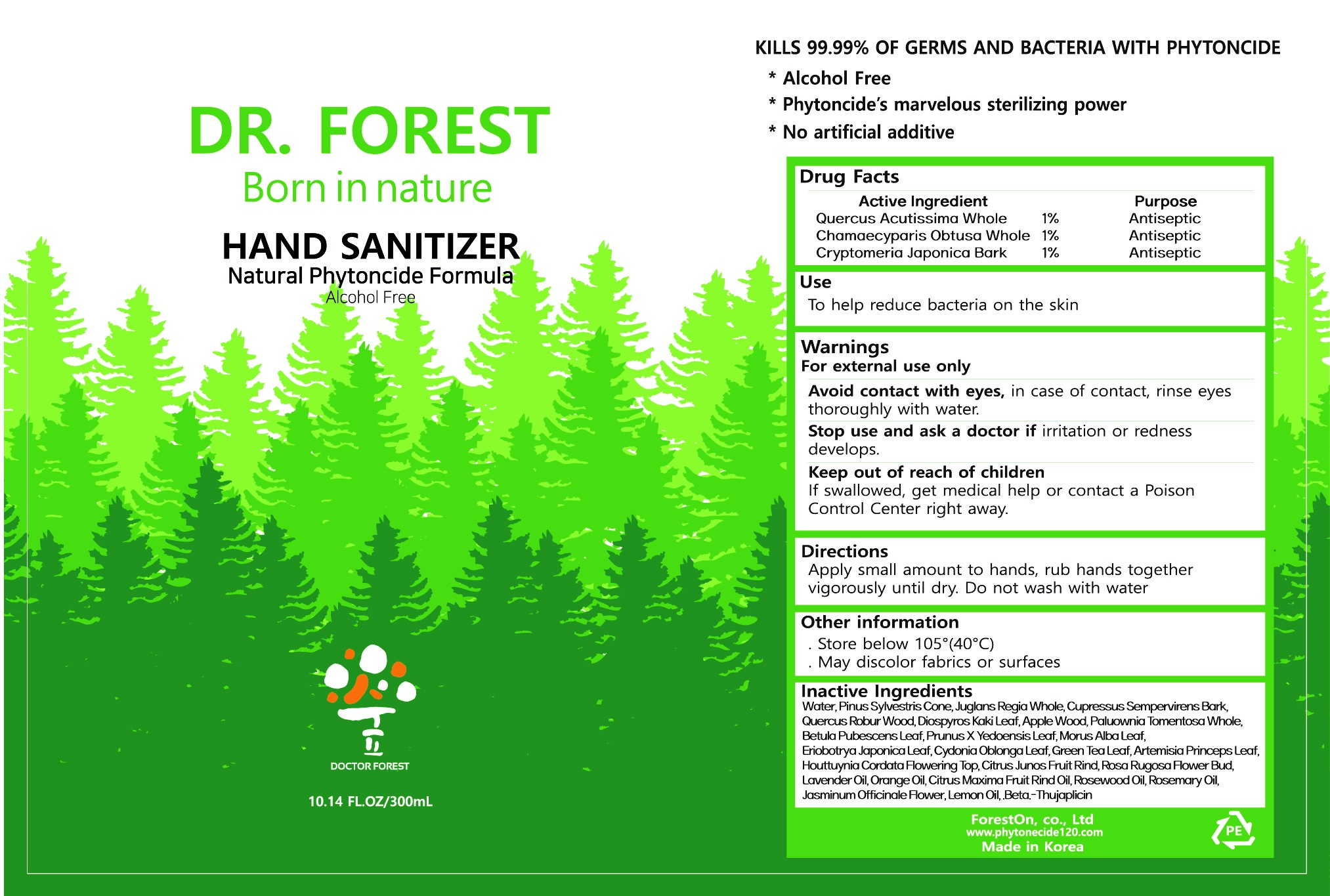 DRUG LABEL: Dr. Forest Hand Sanitizer
NDC: 81609-201 | Form: LIQUID
Manufacturer: Forest On Co., Ltd
Category: otc | Type: HUMAN OTC DRUG LABEL
Date: 20241231

ACTIVE INGREDIENTS: QUERCUS ACUTISSIMA WHOLE 1 mg/100 mL; CRYPTOMERIA JAPONICA BARK 1 mg/100 mL; CHAMAECYPARIS OBTUSA WHOLE 1 mg/100 mL
INACTIVE INGREDIENTS: ARTEMISIA PRINCEPS LEAF; HOUTTUYNIA CORDATA FLOWERING TOP; CITRUS JUNOS FRUIT RIND; .BETA.-THUJAPLICIN; WATER; GREEN TEA LEAF; PINUS SYLVESTRIS CONE; QUERCUS ROBUR WOOD; ROSA RUGOSA FLOWER BUD; ORANGE OIL; ROSEMARY OIL; LEMON OIL; ERIOBOTRYA JAPONICA LEAF; CITRUS MAXIMA FRUIT RIND OIL; APPLE WOOD; ROSEWOOD OIL; CYDONIA OBLONGA LEAF; MORUS ALBA LEAF; PAULOWNIA TOMENTOSA WHOLE; BETULA PUBESCENS LEAF; PRUNUS X YEDOENSIS LEAF; DIOSPYROS KAKI LEAF; LAVENDER OIL; JASMINUM OFFICINALE FLOWER; JUGLANS REGIA WHOLE; CUPRESSUS SEMPERVIRENS BARK

81609-201 Dr. Forest Hand Sanitizer

Active Ingredient

QUERCUS ACUTISSIMA WHOLE 1%

CHAMAECYPARIS OBTUSA WHOLE 1%

CRYPTOMERIA JAPONICA BARK 1%

Purpose

Antiseptic

Use

To help reduce bacteria on the skin

Warnings

For external use only

Avoid contact with eyes, in case of contact, rinse eyes thoroughly with water.

Stop use and ask a doctor if

irritation or redness develops.

Keep out of reach of children

If swallowed, get medical help or contact a Poison Control Center right away.

Directions

Apply small amount to hands, rub hands together vigorously until dry. Do not wash with water

Other information

Store below 105º(40ºC)

May discolor fabrics or surfaces

Inactive Ingredients

WATER, PINUS SYLVESTRIS CONE, JUGLANS REGIA WHOLE, CUPRESSUS SEMPERVIRENS BARK, QUERCUS ROBUR WOOD, DIOSPYROS KAKI LEAF, APPLE WOOD, PAULOWNIA TOMENTOSA WHOLE, BETULA PUBESCENS LEAF, PRUNUS X YEDOENSIS LEAF, MORUS ALBA LEAF, ERIOBOTRYA JAPONICA LEAF, CYDONIA OBLONGA LEAF, GREEN TEA LEAF, ARTEMISIA PRINCEPS LEAF, HOUTTUYNIA CORDATA FLOWERING TOP, CITRUS JUNOS FRUIT RIND, ROSA RUGOSA FLOWER BUD, LAVENDER OIL, ORANGE OIL, CITRUS MAXIMA FRUIT RIND OIL, ROSEWOOD OIL, ROSEMARY OIL, JASMINUM OFFICINALE FLOWER, LEMON OIL, .BETA.-THUJAPLICIN